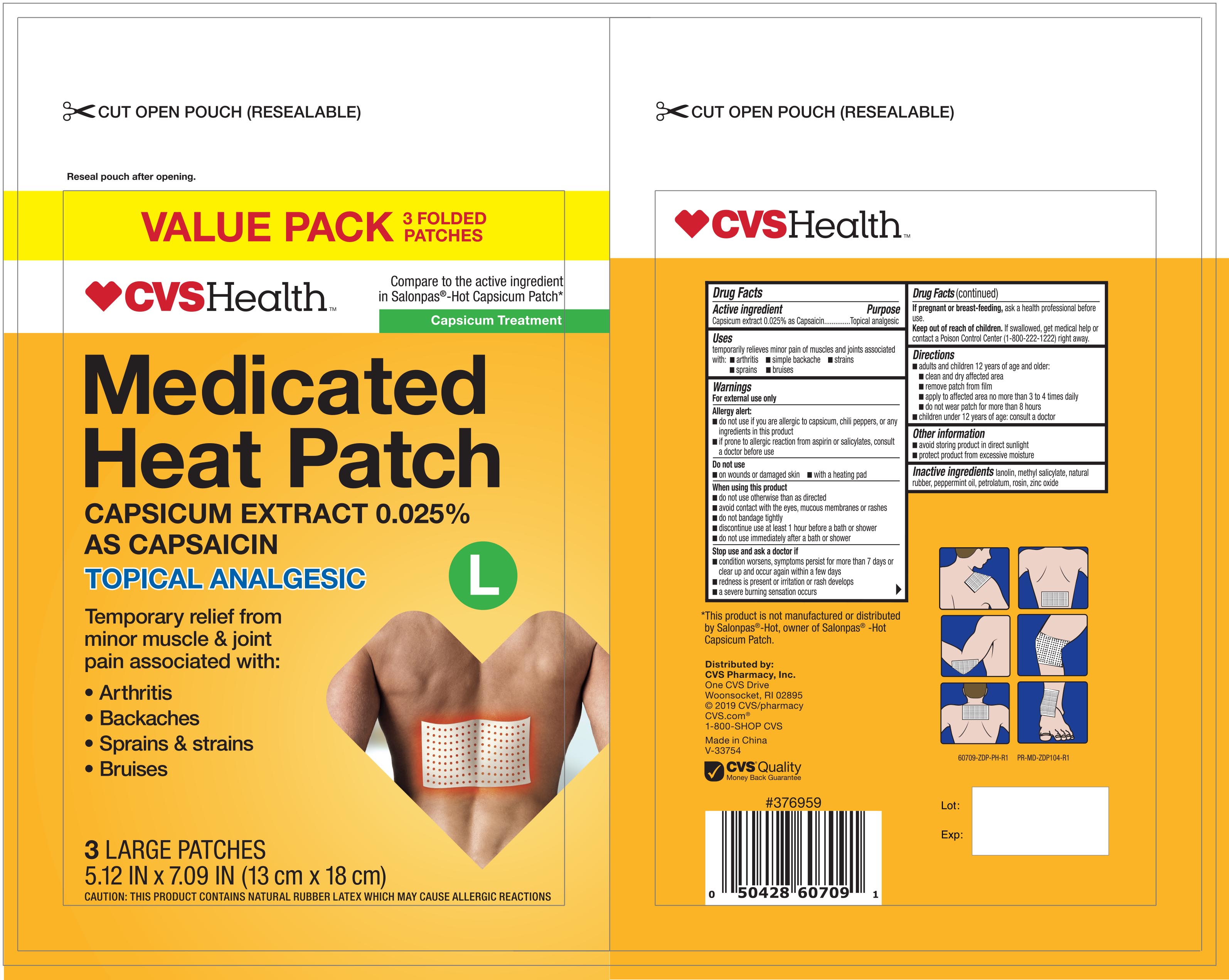 DRUG LABEL: CVS Medicated Heat
NDC: 69842-091 | Form: PATCH
Manufacturer: CVS Pharmacy
Category: otc | Type: HUMAN OTC DRUG LABEL
Date: 20251028

ACTIVE INGREDIENTS: CAPSICUM 0.025 mg/1 1
INACTIVE INGREDIENTS: LANOLIN; PEPPERMINT OIL; PETROLATUM; ZINC OXIDE; ROSIN; METHYL SALICYLATE; NATURAL LATEX RUBBER

CVS Medicated Heat Patch NBE Salonpas Capsicum 3 ct 60709

Active ingredient Purpose

Capsicum extract 0.025% as Capsaicin.....................Topical analgesic

Uses

temporarily relieves minor pain of muscles and joints associated with:

- arthritis
- simple backache
- strains
- sprains
- bruises

Warnings

For External use only

Allergy alert:

- do not use if you are allergic to capsicum, chili peppers, or any ingredients in this product
- if prone to allergic reaction from aspirin or salicylates, consult a doctor before use

Do not use

- on wounds or damaged skin
- with a heating pad

When using this product

- do not use otherwise than directed
- avoid contact with the eyes, mucous membranes or rashes
- do not bandage tightly
- discontinue use at least 1 hour before a bath or shower
- do not use immediately after a bath or shower

Stop use and ask a doctor if

- condition worsens, symptoms persist for more than 7 days or clear up and occur again within a few days
- redness is present or irritation or rash develops
- a severe burning sensation occurs

PREGNANCY OR BREAST FEEDING

If pregnant or breast-feeding, ask a health professional before use.

Keep out of reach of children.

If swallowed, get medical help or contact a Poison Control Center (1-800-222-1222) right away.

Directions

- adults and children 12 years of age and older:
- clean and dry affected area
- remove patch from film
- apply to affected area no more than 3 to 4 times daily
- do not wear patch for more than 8 hours
- children under 12 years of age: consult a doctor

Other information

- avoid storing product in direct sunlight
- protect product from excessive moisture

Inactive ingredients

lanolin, methyl salicylate, natural rubber, peppermint oil, petrolatum, rosin, zinc oxide

DOSAGE AND ADMINISTRATION

Distributed by:

CVS Pharmacy, Inc.

One CVS Drive

Woonsocket, RI 02895